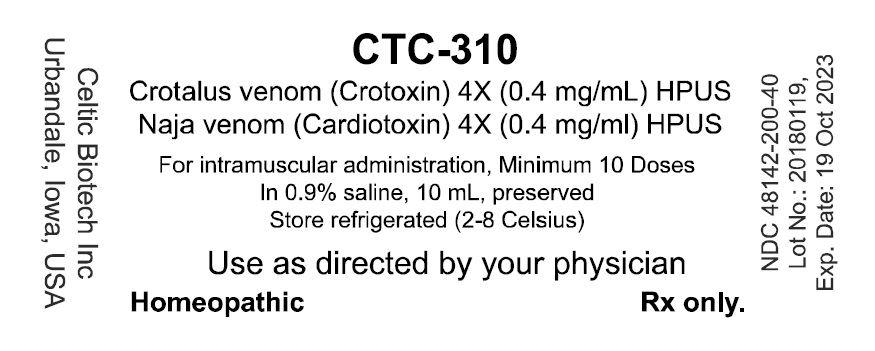 DRUG LABEL: CTC-310
NDC: 48142-200 | Form: INJECTION, SOLUTION
Manufacturer: Celtic Biotech Iowa, Inc.
Category: homeopathic | Type: HUMAN PRESCRIPTION DRUG LABEL
Date: 20180328

ACTIVE INGREDIENTS: CROTALUS DURISSUS TERRIFICUS VENOM 4 [hp_X]/1 mL; CARDIOTOXIN III 4 [hp_X]/1 mL
INACTIVE INGREDIENTS: SODIUM CHLORIDE 9 mg/1 mL; BENZALKONIUM CHLORIDE 0.1 mg/1 mL

DESCRIPTION

CTC-310 is a liquid for injection formula comprising a 1:1 combination of Crotoxin and Cardiotoxin

Crotoxin preparations are made from the venom of the South American rattlesnake, Crotalus durissus.

Cardiotoxin preparations are made from the venom of the Asian cobra Naja naja.

They are homeopathic formulations that include sterile injectables for intravenous and subcutaneous use.

INDICATIONS

According to the FDA reference text “Clarkes’ Materia Medica 1900”;

Crotalus venom preparations are indicated as homeopathic medications for numerous conditions but especially; Cancers. Tongue, inflammation of ; cancer of. Clinical experience shows that Crotoxin also provide relief from some forms of pain.

Cobra venom preparations are indicated as homeopathic medications for several conditions but especially for; angina faucium, angina pectoris, asthma, dysmenia (painful menses), grief (depression), headache (migraine), pain in ovaries (ovarian cysts), spinal irritation (back pain) and sore throat. Cardiotoxin is the principal active analgesic component.

PHARMACOLOGIC CATEGORY

Anti-cancer.

PHARMACOLOGY

The principal active components in both venoms are cytotoxins. Crotoxin (CT) is a pre-synaptic bi-partite beta-neurotoxin with phospholipase A2 (PLA2) activity. Evaluation by the Developmental Therapeutics Program of the National Cancer Institute (NSC 624244) for cytotoxicity in vitro against a panel of human tumour cell lines showed enhanced cytotoxicity towards melanoma, CNS and non-small cell lung cancer lines. Toxin-phospholipid interaction and subsequent accumulation of products of phospholipid hydrolysis in the membrane may alter membrane packing, disrupt lipid domains and affect protein conformation resulting in effects like inhibition of type II Ca^2+ channels or alteration of transmembrane signaling pathways. Current thought suggests that CT binds to the upregulated Crocalbin that is upregulated in malignant cells. The Nicotinic Acetylcholine receptor is also upregulated in tumor cell lines and have been clearly identified as having a role in proliferation especially in lung cancer and CNS tumors – tumor populations with high sensitivity to CT. The released PLA2 produces arachidonic acid at the membrane surface that activates protein kinase C (PKC) and possibly other tyrosine kinases. PKC in turn phosphorylates endogenous caspases and the activated caspases initiate the process of programmed cell death.

The main pharmacological target for Cardiotoxin has not been clearly identified though it has been shown to target heparin sulphate-glyco proteins. Cardiotoxins (CD) have a number of pharmacological properties in intact tissues including hemolysis, cytolysis, contractures of muscle, membrane depolarization and activation of tissue phospholipase C and, to a far lesser extent, an arachidonic acid-associated phospholipase A2. The toxins have also been demonstrated to open the Ca2+ release channel (ryanodine receptor) and alter the activity of the Ca^2++Mg^2+-ATPase in isolated sarcoplasmic reticulum preparations derived from cardiac or skeletal muscle. However, a relationship of these actions in isolated organelles to contracture induction has not yet been established. The toxins also bind to and, in some cases, alter the function of a number of other proteins in disrupted tissues. The most difficult tasks in understanding the mechanism of action of these toxins have been dissociating the primary from secondary effects and distinguishing between effects that only occur in disrupted tissues and those that occur in intact tissue.

PHARMACODYNAMICS

Both actives exert potent cytolytic activities in-vitro. Tissue culture studies were performed using murine and human tumour cell lines. The responses are summarized in Table 1.

Table 1: Comparison of cytotoxicity of CT, CD, and VRCTC-310
Panel | LC50 mg/ml |  |  | Theoretical Additive LC50 | Potent. (factor)
Panel | CT | CD | CTC-310 | Theoretical Additive LC50 | Potent. (factor)
Leukemia | 43.6 | 6.3 | 7.2 | 11.0 | (1.5)
Non Small Cell Lung | 12.7 | 3.9 | 5.0 | 6.0 | (1.2)
Small Cell Lung | 30.1 | 1.15 | 3.9 | 2.2
Colon | 74.9 | 22.4 | 36.4 | 34.5
Central Nervous System | 7.5 | 2.2 | 2.1 | 3.4 | (1.6)
Melanoma | 7.6 | 1.86 | 2.8 | 3.0
Ovaria | 21.0 | 5.4 | 7.3 | 8.6 | (1.2)
Renal | 10.1 | 3.2 | 5.4 | 4.9

Prior data showed that CT-induced cytotoxic effects appeared to be highly selective toward cell lines expressing an upregulated density of Epidermal-like Growth Factor receptors, though CT appeared to unexpectedly promote EGFR phosphorylation. Enhanced EGFR activity in cancer cells and tumors is associated with increased growth, survival and angiogenesis of tumors. CT stimulated phosphorylation of the EGFR is a cellular response to the induction of apoptosis.

CD has poor anti-tumor effect in-vivo but it has recently been discovered the CD can block this rescue mechanism thereby enhancing the cytocidal activity. CD induces apoptosis in adeno-carcinoma A549 cells, as indicated by an increase in the sub-G(1) population, phosphatidyl-serine externalization, loss of mitochondrial membrane potential (Psi(m)) with cytochrome c release and activation of caspases 9 and 3. The signal transduction pathways involved in the effects of CD in A549 cells were evaluated and the results indicated that CD suppresses phosphorylation of EGFR and activation of phosphatidylinositol 3-kinase (PI3-K)/Akt and Janus tyrosine kinase (JAK) 2/signal transducer and activator of transcription (STAT) 3, all of which are downstream molecules in the EGFR signaling pathway. Additional testing suggested that PI3-K is an upstream activator of JAK2/STAT3. Together, the results of the study indicated that CD induces apoptosis in A549 cells by inactivating the EGFR, PI3-K/Akt and JAK2/STAT3 signaling pathways. Similar data was observed for MDA-MB-231 breast cancer cells, a highly metastatic human breast carcinoma cell line in addition to the inhibition of metastasis.

In wound-healing assay, the cell migration of oral squamous cells (Ca9-22 cells) was attenuated by CD in a dose- and time-responsive manner. After CD treatment, the MMP-2 and MMP-9 protein expressions were downregulated, and the phosphorylation of JNK and p38-MAPK was increased independent of ERK phosphorylation. It was determined that CD also has antiproliferative and -migrating effects on oral cancer cells involving the p38-MAPK and MMP-2/-9 pathways.

Secondary Pharmacology

CT can produce flaccid paralysis and death due to paralysis of respiratory muscles. Artificial respiration can keep the animals alive and, provided that the dose is not higher than 1.5 LD50, is followed by recovery. CD is a basic amphipathic peptide of relatively weak lethal toxicity when administered by the i.m. route (LD50 i.m. in mice 52 mg/kg; in rats 65 mg/kg). Strangely, when CT and CD are combined the toxic effects of CT are significantly reduces through an unknown mechanism. Additionally, CT has been reported to exert anti-viral activity which is thought to use a mechanism similar to the anti-tumor pathways.

Animal studies showed that CT administered by parenteral injection exhibited a dose-dependent analgesic action in mice using hot plate test and acetic acid-writhing test. The peak effect of CT analgesia was seen 3 h after its’ administration (in contrast to its pharmacokinetics). CT had significant analgesic action in rat tail-flick test. In the mouse acetic acid-writhing test, intra-cerebral ventricle administration of CT also produced marked analgesic effects. Atropine at 0.5 mg/kg (im) or 10 mg/kg (ip) or Naloxone at 3 mg/kg (ip) failed to block the analgesic effects of Crotoxin. In animal models of neuropathic pain induced by rat sciatic nerve transaction, it was revealed that CT has prolonged activity persisting for up to 64 days. It was found that the analgesia was mediated by activation of central muscarinic receptors and partially, by activation of alpha-adrenoceptors and 5-HT receptors.

CD’s antiproliferative activity is exerted through mechanisms associated with inflammatory activity so it is consistent that CD exhibits analgesic and anti-inflammatory activity. CD has been shown to be effective in animal models of acute, chronic and neuropathic pain including rheumatoid arthritis. It has also be found be orally bioavailable. It is reported to ameliorate kidney injury in several CKD animal models and potentiates the release of insulin from pancreatic cells.

CONTRAINDICATIONS

CTC-310 is intended to be used as a monotherapy. Clinical experience suggests that concurrent use of radio- or chemotherapy may inhibit the activity of the drug. As the known receptors include those sensitive to nicotine is it is likely that nicotine will inhibit the activity of Crotoxin.

PRECAUTIONS

PREGNANCY

Pregnancy: No significant data has been collected on the use of Crotoxin during pregnancy. No animal reproduction studies have been conducted to assess the effects of Crotoxin on the developing fetus.

NURSING MOTHERS

Nursing mothers: It is not known whether this drug is distributed into breast milk. Crotoxin is not orally bioavailable therefore it is unlikely to have any detrimental effects

PEDIATRIC USE

Pediatric use: There is no information on the use of Crotoxin in children and young adults.

INTERACTIONS

No detailed reports of drug interactions have been reported.

ADVERSE REACTIONS

The majority of reported adverse effects associated with CTC-310 result from Crotoxin’s neurotoxic effects.

In clinical studies with CTC-310, subjects reported the following dose related adverse effects; anxiety, increased blood pressure, diplopia, nystagmus and strabismus.

SERIOUS ADVERSE REACTIONS

With the injection of CTC-310, allergic reactions, sometimes severe (anaphylactic), have been reported. Anaphylaxis manifests usually within 30 minutes of administration. The use of antihistamines was found to alleviate the allergic reaction. Co-administration of antihistamines is advised.

FORMATS

CTC-310 is supplied in a solution of 0.9% saline for injection, at a concentration of 0.4mg/ml of each active with 0.01% benzalkonium chloride as a preservative. Dilution of this solution with saline for injection (SFI) can be useful for the initiation of therapy by subcutaneous injection in addition to tolerising the patient and their immune system to the drug. Always follow your health practitioner’s instructions.

DOSAGE AND ADMINISTRATION

The maximum reported tolerable dose of CTC-310 by intramuscular bolus injection is 0.017 mg/Kg. Injection site reactions are common though will subside in 2-3 weeks with continued use. With dose escalation procedures doses of 0.023 mg/Kg have been attained. Subcutaneous administration may be easier and more comfortable that intramuscular without any likely loss in activity.

STORAGE

CTC-310 should be stored refrigerated (2-10°C / 38-50 °F).

STABILITY

For maximum shelf life, the product should be stored at 4°C when not in use though shipping at transient ambient temperatures (10-30 °C) is not expected to significantly affect the product. CTC-310 is potent for a period in excess of 60 months when stored as directed.

Do not store at room temperature or strong sources of lights. Do not freeze or expose to high heat.

SAFETY INFORMATION

The toxic effects of CTC-310 are associated with CT. Paradoxically, CD reduces CT’s over toxicity.

Neurological: CT exerts analgesic activity presumed to be in the CNS despite the suggestion in pharmacokinetics studies that CT does not accumulate in the brain. Intracerebroventricular administration of CT to mice and rats yielded analgesic responses and was not toxic to the exposed nerve cells at the doses tested. In other studies CT appeared to increase the anxiety level in rodents. It is assumed that CT exerts these effects through peripheral pathways.

Cardiovascular: CT has no direct effects on the heart in-vivo. Rat hearts showed no response to the presence of CT though it is the most resistant species to this neurotoxin. In Guinea pigs, which have a high sensitivity to CT, no effect was noted in the heart unless protein was removed from the perfusion solution. At this point the contractile force of the heart was reduced by approximately 25%, reported to be a consequence of non-specific binding that occurred in the absence of albumin. No impact (NOEL) on heartbeat was noted at doses of 0.25mg/kg. Studies on the cardiovascular effects in anaesthetized dogs demonstrated that CT induced a transient and minor reduction (20%) in blood pressure on administration. With the administration of sequential doses of CT, the animal became resistant to the vascular effects of CT.

Respiration: CT is characterized by its ability to induce respiratory paralysis at high doses through blockade at the neuromuscular junction of the phrenic nerve. However, no respiratory effects were observed with the use of CT at 0.25 mg/Kg in dogs (maximum human dose is <0.015 mg/Kg). This would demonstrate a clear dose relationship between a NOEL and overt respiratory failure. In cases where respiratory paralysis was induced, the animal’s survival could be assured with the use of artificial ventilation. Crotoxin’s direct effects on the phrenic diaphragm has been well-established and provided the mechanism by which crotoxin interferes with respiration. Furthermore, it has been established that resistance to the toxic effects of Crotoxin are located at this site and resistance can be induced using low doses of Crotoxin.

Renal: The effects of Crotalus durissus terrificus venom and CT were studied on glomerular filtration rate (GFR), urinary flow (UF), perfusion pressure (PP) and percentage sodium tubular transport (%TNa+). The infusion of Crotalus durissus terrificus venom (10 microg/ml) and CT (10 microg/ml) increased GFR (control = 0.78 +/- 0.07, venom = 1.1 +/- 0.07, CT = 2.0 +/- 0.05 ml g(-1) min(-1), P<0.05) and UF (control = 0.20 +/- 0.02, venom = 0.32 +/- 0.03, CT = 0.70 +/- 0.05 ml g(-1) min(-1), P<0.05), and decreased %TNa+ (control = 75.0 +/- 2.3, venom = 62.9 +/- 1.0, CT = 69.0 +/- 1.0 ml g(-1) min(-1), P<0.05). The infusion of crude venom tended to reduce PP, although the effect was not significant, whereas with CT PP remained stable during the 100 min of perfusion. The kidneys perfused with crude venom and CT showed abundant protein material in the urinary space and tubules. It was concluded that Crotalus durissus terrificus venom and CT, its major component, caused acute nephrotoxicity in the isolated rat kidney. The current experiments demonstrated a direct effect of venom and CT on the perfused isolated kidney.

All in-vivo pharmacological studies have shown the toxic effects of CT to be reversible.

Chronic rodent toxicity studies with CTC-310

The LD50 of CTC-310 in mice after a single i.p. injection is approximately 0.45 mg/kg; the LD50 for i.m. administration is 0.93 mg/kg. When compared with the i.p. values for CT (0.095 mg/kg) and CD (1.7 mg/kg), the combined CTC-310 results in a 2.5-fold decrease specifically in CT-mediated neurotoxicity. Thus, the addition of the non-neurotoxic CD provides protection against the neurotoxic effects of CT. Different ratios were tested in vivo, and the optimal molar ratio was CD 3:1 CT (with a 1:1 mass ratio).

To evaluate the toxicity of CTC-310, 10 Sprague-Dawley rats were implanted with intraperitoneal slow-release devices and subjected to treatment with 0.5 microgram/g body weight/d for 14 days. Biochemical evidence at days 7 and 14 showed blood, muscular, renal and metabolic disturbance, mostly reversed by day 28. No significant changes were found in necropsy.

To assess i.v. administration of CTC-310 in rabbits, ten animals were subjected to surgical implant of fixed jugular catheter, by which they received daily IV doses of 0.03 mg/kg body weight of CTC-310 for 30 days (n = 8) or saline (n = 2). The procedure was well tolerated in all rabbits. One of the animals died after the sixth dose of VRCTC-310 with CNS involvement; two additional rabbits required dose-reduction. All other rabbits achieved 30 days of treatment and were sacrificed. All rabbits (even controls) developed lymphocytosis and mild anaemia, without changes in blood neutrophils. No changes were found in serum transaminases (GOT and GPT), cholesterol, triglycerides, and y-glutamyl transpeptidase. At necropsy, chronic granulation tissue was found surrounding the implant in all rabbits. CTC-310-treated rabbits presented generalised and marked swelling of hepatocytes, with areas of cytoplasmic vacuolisation. No abnormalities were found in kidney, heart, lung, spleen, adrenal gland, uterus, testes and ovary.

Acute and subchronic toxicities of CTC-310 have been studied in Beagle dogs. Single i.m. doses of 0.25, 0.5 and 1.0 mg/kg resulted in dose-dependent local muscular toxicity consisting of myofiber atrophy, interstitial edema and macrophage infiltration. AST, ALT and LDH levels also increased on day 2, returning to normal values on days 6-8. Local lesions were absent after recovery on day 45. At 2.0 mg/kg, signs of neurotoxicity (ataxia) appeared, in addition to vomitus, salivation, hematuria and myotoxicity in tongue and diaphragm on day 8. Local lesions healed with fibrosis at the site of injection on day 45. Administration of fixed (0.025 and 0.05 mg/kg) or escalating (0.025-0.1 mg/kg) daily doses for 30 days also produced local muscular damage, which was absent at day 75. The increases in AST, ALT and LDH serum activities on days 2-4 were independent of dosing schedule and sharply decreased on day 8, despite continuation of treatment. An escalating dose schedule of 0.025-2.0 mg/kg showed local muscle damage at the site of injection on day 31, however, there were no lesions of myotoxicity in the tongue or diaphragm and no clinical signs of neurotoxicity were observed. Animals tolerated the subchronic treatment better than the acute. The resolution of serum enzymes to normal values during treatment may be attributed to a decrease of sensitivity to CTC-310-mediated myotoxic effects.

There is no explanation for the unexpected reduction in overt toxicity when CT was combined with CD. Within the outlined toxicity studies the manifestation of toxic effects in animals (rabbits, cats, dogs and monkeys) using CT or CTC-310 were consistent implying that the majority of effects were contributed specifically by CT. CD served only to permit higher doses of CT be administered – thereby suggesting CD did not mask CT’s neurotoxic effects in-vivo. However, this is clearly a positive effect when it comes to the use of the product in humans. There is no evidence that CD masks other symptoms as the outcomes from toxicity studies for both products appear identical. Human experience does not reveal any subtle differences between the two products in the side-effect profile.

Pharmacokinetics

Studies on organ distribution of ^125I-CT show that 1h after the intravenous injection into mice only 5% remains in plasma, while major amounts are found in liver (16%), kidneys (8.26%) and the carcass (48%). About 9% is excreted with the urine in three hours. Two hours after injection the liver contain 12% of the amount injected, kidney 3% and the carcass 22%. After 26 h only 12% of the radioactivity injected remains, mainly in liver.

Disposition of CT administered i.v. at the doses of 0.045 and 0.06 mg/kg was also followed by double-sandwich ELISA amplified by avidin-peroxidase. Plasma concentrations of CT fell rapidly in the first hour and then slowly up to a level below the detection limit of the assay 18h after injection. Disposition was consistent with a two-compartment open model with half-lives of 6.4 ± 0.4 min for the α-phase and 4.8-5.2 h for the β-phase. The AUC was 12 ± 1.9 µg.min.ml^-1.

Following the intramuscular injection of CT at 0.1 mg/kg, there is a rapid absorption of toxin from the injection site, reaching a peak (50-60 ng/ml) 10-15 min after injection. The half-lives of the α and β phases were 23 ± 4 min and 4.7 ± 0.3 h, respectively. However, the AUC was 7.0 ±1.0 µg min.ml^-1, i.e., smaller than that obtained for i.v. injection of a smaller dose. This may indicate that absorption from the injection site is rapid but incomplete, the toxin bound to muscular tissue being slowly released.

Reproduction and Teratogenicity

The effects of CTC-310 in reproduction have notyet been completed. As CTC-310 is intended to treat cancer it would suggest that the drug could adversely affect rapidly dividing cells and active contraception should be practiced with the drug’s use.

Local Tolerance

CTC-310 causes injection site reactions when injected s.c. or i.m. due to its myotoxic action. In humans, these reactions subside with repeated administration over the course of 2-3 weeks.

CLINICAL EXPERIENCE

Pure CT and CT/Cardiotoxin (CTC-310) formulations have been through 6 clinical investigations. The results of five of these studies have been published in scientific journals. The results from each condensed into table 1 and briefly summarized below. While CT is the principle active agent of interest the drug has been employed alone and in combination with CD, CD may allow the patient avoid the longer dose escalation phase of CT alone, and be more useful in subjects with advanced disease.. With that said, both products have been employed in human Phase I studies as listed in Table 2 & 3.

Table 2: Human Clinical Oncology Studies.
Product | Indication | No. of patients | Duration | Route | Drug ADR
CTC-310 | Cancer | 15 | 30 days | i.m. | 2 anaphylactic reactions
CTC-310 | Cancer | 5 | 8 weeks | i.t. & p.t. | Not available
CT | Cancer | 23 | 30 days, longest 117 days | i.m. | 1 anaphylactic reaction
CT | Cancer | 6 | Longest 75 days | i.v. | None reported
CT | Cancer | 6 | 54 days | i.v. | grade 1 to 2 drug-related events of anorexia, diplopia and nystagmus.
CT | Cancer | 6 | 35 days | i.v. | None reported
i.m.; intramuscular, i.t.: intratumour, p.t.; peri-tumour, i.v.; intravenous

A phase I study was performed to evaluate the maximum tolerated dose (MTD), safety profile and pharmacokinetic data with CTC-310 (Costa et al., 1997). Fifteen patients with refractory malignancies were entered after providing written informed consent. CTC-310 was administered as an intramuscular injection daily for 30 consecutive days. Doses were escalated from 0.0025 to 0.023 mg/kg. Toxicities included local pain at the injection site, eosinophilia, reversible diplopia and palpebral ptosis. Dose escalation was stopped at 0.023 mg/kg, when two patients had developed anaphylactoid reactions. Both cases had high drug-specific IgG by EIA. MTD was 0.017 mg/kg and the recommended dose for phase II studies is 0.017 mg/kg. Stabilization was found in six patients.

From December 1996 to August 1997, five patients with histologic confirmed local advanced cancer (breast cancer 3, squamous cell cancer of the hand 1, chordoma 1) were treated at Bernardo Houssay Hospital, Oncology Unit with CTC-310, at the full dose of 0.014 mg/kg once a week, inoculated peritumorally and distributed into four different injections around the tumor, for no less than eight courses. All patients gave written informed consent according to local ethics committee requirements (Costa et al., 1998).

Table 3: Cancer types observed in treated Subjects and disease response.
Reference | Product | Dose | Cancer types involved
Plata et al. 9 patients | CT | 0.3mg/ m^2 (0.009mg/Kg) i.m & i.t Daily | Breast (2 CR), Pancreas (2 PR), liposarcoma (1 PR), Mesothelioma (1 PR), Fusocellular sarcoma (1 PR), Glioma (1 PR), Orbital adenocarcinoma (1 PR)
Costa et al. 1997 15 patients | CTC-310 | 0.0025-0.023 mg/Kg i.m. Daily | NSCLC (1 PR, 1 PD), Breast (2 SD, 1PD), Laryngeal (1 SD), Cervical (1 SD, 1 PD), Ovarian (1 SD), Stomach (PD), Pancreas (1 PD), Gall bladder (1 PD), Colon (1 PD), Rectum (1 SD), Maxilla (1 PD)
Costa et al. 1998 5 patients | CTC-310 | 0.014mg/Kg i.m. Weekly | Breast (2 CR, 1PR), Squamous cell (1 CR), Chordoma (1 PR)
Hawkins 6 patients | CT | 0.03mg/m^2 (0.0009mg/Kg) i.m. Weekly | Colon cancer (4 PD), Pancreatic (2 PD)
Cura et al. 23 patients | CT | 0.03-0.22 mg/m^2 (0.0009-0.007mg/Kg) i.m. Daily | Breast (1 CR, 2 PD), Rectal (1 PR), larynx (1 PR), Thyroid (1 PR), Fibrosarcoma (1 SD), Bladder (1 PD), Cervix (2 PD), Gastrointestinal (6 PD), NSCLC (3 PD), Head & Neck (1 PD), Fallopian (x1), Ewing sarcoma (1 PD), Liposarcoma (1 PD)
Medioni et al 6 patients | CT | 0.04-0.32 mg/m^2 i.v. over 2 hr, 5 of 7 days per week. | Colorectal Lieberkuhnian adenocarcinoma (PD), epithelioid mesothelioma (PD), non-small-cell lung cancer (PD), carcinoma of the unknown primary site (PD), invasive ductal carcinoma (PD) and ovarian papillary adenocarcinoma (PD).
Delgado et al 6 patients | CT | 0.04-0.32 mg/m^2 i.v. pump, 7 days per week. | Nasal squamous cell carcinoma (SD), glioblastomas (PD), endometrial adenocarcinoma (PD), NSCLC (PD) and prostatic carcinoma (SD)
TOTAL | 70 subjects |  | 7 SD, 13 PR, 8 CR

A complete response was observed in 3 pts (breast cancer 2, skin carcinoma of the hand 1), and a partial response was registered for the other two pts. The patient with local-advanced breast cancer (carcinoma en cuirasse) who was inoculated intra-and-peritumoral with CTC-310 for 6 weekly courses (0.014 mg/kg/week) with the drug had a >80% reduction in tumor. A 133 days follow-up demonstrated not only an objective complete response of the primary tumor mass, but the disappearance of supraclavicular tumor mass as well a significant reduction in lymphangitis. No toxicities were observed, except for a mild local pain at the site of the injection. It was concluded that weekly CTC-310 given by subcutaneous, peritumoral route is an active treatment for advanced skin metastatic tumors that is well tolerated and safe.

Phase I clinical trials of CT (Cura et al., 2002) was performed at the Hospital “General San Martìn” (Universidad Nacional de Rosario), Paranà, Entre Rìos. According to the protocol approved by the National Administration of Foods, Medicines and Medical Technology (A.N.M.A.T, Argentina), twenty six patients with solid tumours refractory to conventional therapy were admitted after signing a written informed consent. Twenty three patients were evaluated after the administration of CT as a daily intramuscular injection for 30 consecutive days (1-3 cycles) at doses from 0.03 to 0.22 mg.m^-2. No drug-related deaths occurred in this study. Reversible (non-limiting) neuromuscular toxicity (Grades I to II) with diplopia and palpebral ptosis resulting from self-limited paresis of the external ocular muscles due to neuromuscular toxicity was the most characteristic side effect observed starting at the dose of 0.18 mg/m^2.

Strabysmus and/or nystagmus appeared at 0.22 mg/m^2. Patients complained by the discomfort during nystagmus episodes and no further increase in dose were considered. At the doses employed, neuromuscular toxicity did not impair the function of intrinsic ocular musculature and never extended to other muscular groups. No impairment of pharyngeal or laryngeal muscles was observed. Dysphonia, dysphagia, disartria or changes in FVC, suggesting drug related involvement of respiratory muscles were consistently absent (Cura et al., 2002). Neuromuscular toxicity did not require any dose adjustment and disappeared after one to three weeks even continuing the treatment. Except for transient increases (Grades I-III) in the levels of aminotransferases and creatinine kinase attributable to CT myotoxicity (Table III.1.3.1.5.2d), no other drug-related limiting toxicities were observed.

A Phase I clinical study with CT was completed at the George Pompidou Hospital (Paris, France). Titled as an “Open Label Phase I Clinical Trial of Crotoxin in Patients with Advanced Cancer using an Intravenous Route of Administration,– designed to be conducted in two cohorts, cohort 1 was conducted with six patients (one male and five females) with advanced solid tumors and no further therapeutic options (Medioni et al, 2017). The primary objectives of the cohort 1 study was to; 1. Confirm that human subjects can be made tolerant to i.v. CT; 2. Assess the safety and tolerability of CT administered i.v. to Stage IV cancer patients using intra-patient dose escalation procedure; 3.Define Maximum Tolerated Dose (MTD) associated with intra-patient dose escalation. The secondary objectives of the study were to determine the frequency and titer of anti-CT antibodies, document any objective anti-tumour responses and assess if CT could affect analgesic activity: evaluated using questionnaire filled by patients during daily infusions.

Cohort dose escalation was planned once per week, with weekends off. Crotoxin was administered to subjects as out-patients daily by i.v. administration at the hospital over a 2-hour period by saline drip. Patients received Polaramine 10 mg i.v. (antihistamine) before CT administration and Ranitidine 50mg (anti-emetic) intravenously prior to treatment to minimize the potential for anaphylaxis. The escalation schedule extended over 54 days, with dose increased from 0.04 to 0.32 mg/m^2. The patients were monitored daily at the clinic for the duration of the infusion (2 hours) and observed for 30 min following the infusion for adverse reactions. A total of 15 patients were screened and 6 were enrolled. Patients were treated with 8 cycles of Crotoxin administered i.v. over 2h daily, 5 days out of 7, with weekly intra-patient dose escalation. Dose escalation started at 0.04 mg/m^2/day and the last dose was 0.32 mg/m^2/day. Dose escalation extended over a period of 54 days (8 weeks).

For Serious Adverse Events (SAEs) unrelated to the study drug there were none in Patient 001, Patient 003 & Patient 004 (Medioni et al., 2018). Patient 002 experienced Anemia at dose level 6 (0.24 mg/m^2/day) at day 37, grade 3, unrelated, reported as SAE, not reported as (Sudden Unexpected Serious Adverse Reaction (SUSAR), study drug was interrupted for 1 day. Patient 005 experience Hypoxia at dose level 5 (0.20 mg/m^2/day) at day 29, grade 3, unrelated, reported as SAE, not reported as SUSAR. The study drug dose was not changed though treatment and hospitalization was required. Also, sepsis grade 4 and confusion grade 2 at dose level 5 (0.20 mg/m^2/day) at day 35, unrelated, reported as SAE, not reported as SUSAR, patient died 2 days after stopping the study. Patient 006 also experienced Hypoxia at dose level at dose level 3 (0.12 mg/m^2/day) at day 17, grade 2, unrelated, reported as SAE, not reported as SUSAR study drug dose not changed though treatment and hospitalization was required. Fever was reported at dose level 6 (0.24 mg/m^2/day) at day 43, grade 1, unrelated, reported as SAE, not reported as SUSAR, study drug dose was interrupted for 1 day requiring treatment and hospitalization.

Table 3. Summary of Cohort 1 Adverse Event during Study
Subject no | Unrelated to study drug |  | Related to study drug |  | Total
 | AE | SAE | AE | SAE
001 | 9 | 0 | 4 | 0 | 13
002 | 11 | 1 | 0 | 0 | 12
003 | 8 | 0 | 0 | 0 | 8
004 | 25 | 0 | 1 | 0 | 26
005 | 22 | 3 | 0 | 0 | 25
006 | 15 | 2 | 1 | 0 | 18

There were no reported SAEs or SUSARs related to the study drug. Adverse Events (AEs) related to the study drug were not reported in Subjects 002, 003 & 005. Diplopia and nystagmus were the most common. For those patients for whom pain was reported appeared to experience relief when CT was administered. The analgesic effect in all subjects appeared to dissipate during the weekends when no drug was being administered. The reported analgesic activity of Crotoxin in the Cura et al study (2002) was confirmed. All six patients presented Progressive Disease potentially due to the slow dose escalation protocol. It was established that intra-patient dose escalation of Crotoxin was safer than simple bolus administration.

Part 2 of the Phase I study was recently completed at the University Hospital Pitié-Salpêtrière (Paris, France). It followed design of Medioni et al (2017) in intra-patient dose escalation study to treat six patients (5 males and 1 female) with advanced solid tumours and no further treatment options: 1 nasal squamous cell carcinoma, 2 glioblastomas, 1 endometrial adenocarcinoma, 1 NSCLC and 1 prostatic carcinoma (Gil-Delgado et al., 2018). Lightweight Rythmic™ pump capable of continuous delivery (no weekend breaks) allowed patients to stay at home. Dose escalation from 0.08 to 0.64 mg/m^2/day over 35 days and was carried on Mondays, Wednesdays and Fridays, followed by 2h observation at the clinic. Two of 6 patients developed possibly drug-related G1 diplopia and 1/6 pts increased ASAT/ALAT. One patient recruited with pre-existent diarrhoea syndrome with uncontrolled G2 hypomagnesaemia, G3 hypokalaemia and G2 anaemia, developed complete arrhythmia with asymptomatic atrial fibrillation that resolved with amiodarone. Patient was hospitalised for observation and the event was classified as a possible study drug-related SAE as well as related to the digestive syndrome and tubulopathy resulting from previous chemotherapy (nivolumab and platinum salts). It was concluded CT dose escalation is safe but too slow, doses achieved too low and too late for advanced pts. However, stable disease was observed in 2/6 patients and no DLT or MTD were reached.

Overall, of the 70 subjects recorded as having been treated with CT or CTC-310, 8 have had complete remissions, 13 had partial responses and 8 had stable disease. These outcomes were achieved in the absence of optimized treatment programs.

CLINICAL REFERENCES

1. Costa LA, Miles F, Diez RA, Araujo CE, Coni Molina CM and Cervellino JC; Phase I study of VRCTC310, a purified phospholipase A2 purified from snake venom, in patients with refractory cancer: safety and pharmacokinetic data, Anticancer Drugs 8 (9), 829-34 (1997)
2. Costa LA, Miles F, Araujo CE, and Villaruba VG. Intratumoral therapy with VRCTC-310 for refractory skin metastatic breast cancer. Preliminary report. Euro J. Cancer, 34, suppl 5, pg S22 (1998)
3. Costa LA, Fornari MC, Berardi VE, Miloes HA and Diez RA; In vivo effect of snake phospholipase A2 (CT + Cardiotoxin) on serum Il-1alpha, TNF-alpha and IL-1ra level in humans, Immunol Lett, Jan 1, 75(2), 137-41 (2001).
4. Cura, JE, Blanzaco DP, Brisson CB, Cura MA, Cabrol R, Larrateguy L, Mendez C, Sechi JC, Silveira JS, Theiller E, deRoodt AR, Vidal JC. Phase I and Pharmocokinetic study of Crotoxin (Cytotoxic PLA2, NSC-624244) in Patients with Advanced Cancer. Clinical Cancer Research, Vol. 8, 1033-1041 (2002).
5. Gil Delgado M, Bray DH, Delgado FM, Spano JP, Gougis P, Brentano C, Idbaih A, Reid P, Benlhassan K, Diaw K, Khayat D.. Continuous i.v. CROTOXIN in advanced cancer: intra-patient dose escalation, AACR abstract, 2018 accepted
6. Medioni J, Brizard M, Elaidi R, Reid PF, Benlhassan K, Bray D. Innovative design for a phase 1 trial with intra-patient dose escalation: The Crotoxin study. Contemp Clin Trials Comm 7 (2017): 186-168
7. Medioni J, Brizard M, Elaidi R, Reid PF, Benlhassan K, Bray D. Innovative design for a Phase 1 trial with intra-patient dose escalation: the Crotoxin study. AACR abstract, 2018 accepted